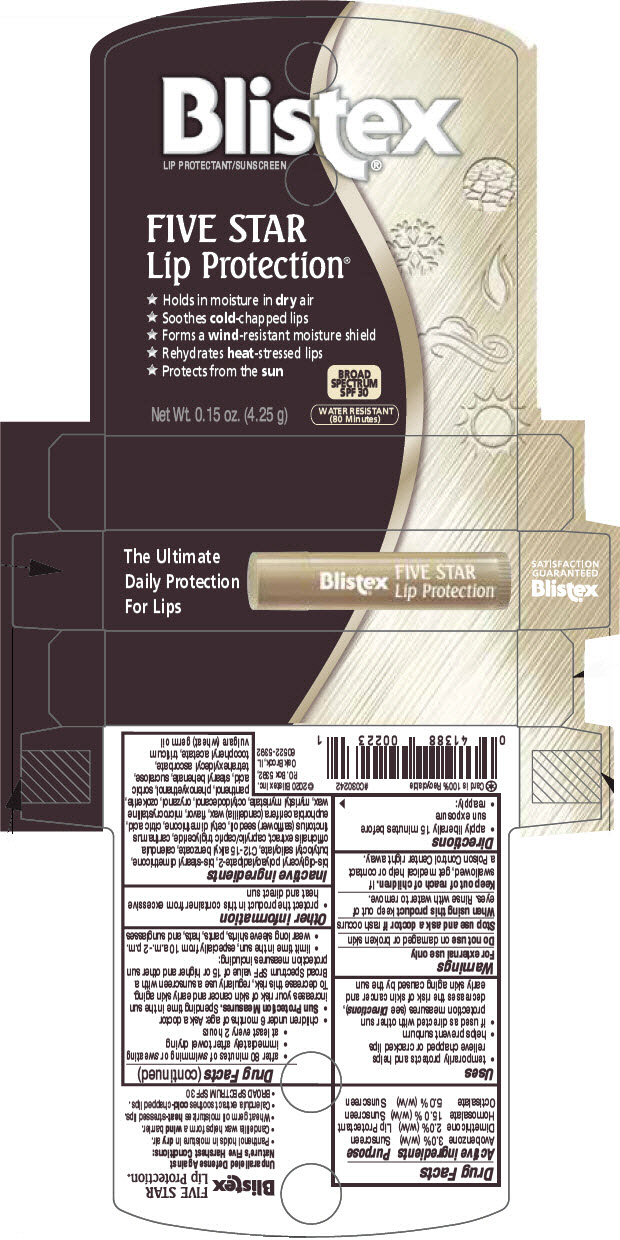 DRUG LABEL: Blistex 
NDC: 10157-1171 | Form: STICK
Manufacturer: Blistex Inc.
Category: otc | Type: HUMAN OTC DRUG LABEL
Date: 20241210

ACTIVE INGREDIENTS: Homosalate 15 g/100 g; Octisalate 5 g/100 g; Avobenzone 3 g/100 g; Dimethicone 2 g/100 g
INACTIVE INGREDIENTS: MICROCRYSTALLINE WAX; CERESIN; OCTYLDODECANOL; BUTYLOCTYL SALICYLATE; ALKYL (C12-15) BENZOATE; MYRISTYL MYRISTATE; STEARYL BEHENATE; CETYL DIMETHICONE 25; STEARYL DIMETHICONE (400 MPA.S AT 50C); BIS-DIGLYCERYL POLYACYLADIPATE-2; CANDELILLA WAX; ORYZANOL; .ALPHA.-TOCOPHEROL ACETATE; TETRAHEXYLDECYL ASCORBATE; PHENOXYETHANOL; MEDIUM-CHAIN TRIGLYCERIDES; CALENDULA OFFICINALIS FLOWER; SAFFLOWER OIL; WHEAT GERM OIL; SUCRALOSE; CITRIC ACID MONOHYDRATE; SORBIC ACID; PANTHENOL

Blistex®
Five Star Lip Protection® Broad Spectrum

Drug Facts

ACTIVE INGREDIENT

Active ingredients | Purpose
Avobenzone 3.0% (w/w) | Sunscreen
Dimethicone 2.0% (w/w) | Lip Protectant
Homosalate 15.0 % (w/w) | Sunscreen
Octisalate 5.0 % (w/w) | Sunscreen

Uses

- temporarily protects and helps relieve chapped or cracked lips
- helps prevent sunburn
- if used as directed with other sun protection measures (see Directions), decreases the risk of skin cancer and early skin aging caused by the sun

Warnings

For external use only

Do not use on damaged or broken skin

Stop use and ask a doctor if rash occurs

When using this product keep out of eyes. Rinse with water to remove.

Keep out of reach of children. If swallowed, get medical help or contact a Poison Control Center right away.

Directions

- apply liberally 15 minutes before sun exposure
- reapply:
  - after 80 minutes of swimming or sweating
  - immediately after towel drying
  - at least every 2 hours
- children under 6 months of age: Ask a doctor
- Sun Protection Measures. Spending time in the sun increases your risk of skin cancer and early skin aging. To decrease this risk, regularly use a sunscreen with a Broad Spectrum SPF value of 15 or higher and other sun protection measures including:
  - limit time in the sun, especially from 10 a.m.-2 p.m.
  - wear long sleeve shirts, pants, hats, and sunglasses

Other information

- protect the product in this container from excessive heat and direct sun

Inactive ingredients

bis-diglyceryl polyacyladipate-2, bis-stearyl dimethicone, butyloctyl salicylate, C12-15 alkyl benzoate, calendula officinalis extract, caprylic/capric triglyceride, carthamus tinctorius (safflower) seed oil, cetyl dimethicone, citric acid, euphorbia cerifera (candelilla) wax, flavor, microcrystalline wax, myristyl myristate, octyldodecanol, oryzanol, ozokerite, panthenol, phenoxyethanol, sorbic acid, stearyl behenate, sucralose, tetrahexyldecyl ascorbate, tocopheryl acetate, triticum vulgare (wheat) germ oil

PRINCIPAL DISPLAY PANEL - 4.25 g Cylinder Blister Pack

The Ultimate
Daily Protection
For Lips

Blistex®

FIVE STAR
Lip Protection®